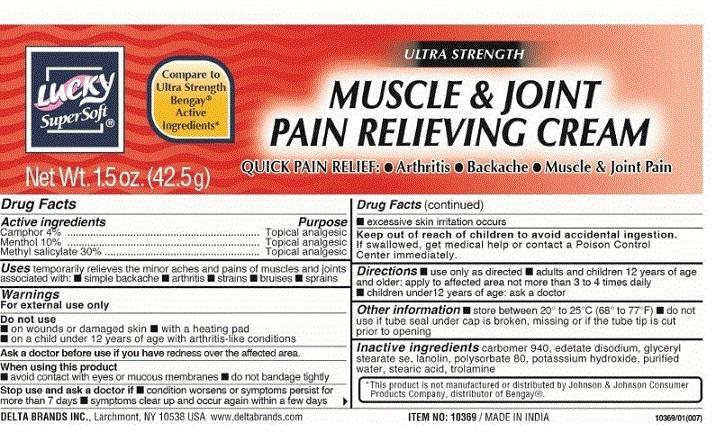 DRUG LABEL: Lucky SuperSoft
NDC: 47046-177 | Form: CREAM
Manufacturer: Anicare Pharmaceuticals Pvt. Ltd.
Category: otc | Type: HUMAN OTC DRUG LABEL
Date: 20201220

ACTIVE INGREDIENTS: CAMPHOR (NATURAL) 4 g/100 g; MENTHOL 10 g/100 g; METHYL SALICYLATE 30 g/100 g
INACTIVE INGREDIENTS: CARBOMER HOMOPOLYMER TYPE C (ALLYL PENTAERYTHRITOL CROSSLINKED); EDETATE DISODIUM; GLYCERYL STEARATE SE; LANOLIN; POLYSORBATE 80; POTASSIUM HYDROXIDE; STEARIC ACID; TROLAMINE; WATER

Muscle and joint pain relieve

Active ingredients

Camphor 4%

Menthol 10%

Methyl Salicylate 30%

Purpose

Topical analgesic

Topical analgesic

Topical analgesic

Uses

temporarily relieves the minor aches and pains of muscles and joints associated with :

■ simple backache ■ arthritis ■ strains ■ bruises ■ sprains

Warnings

For external use only

Do not use

■ on wounds or damaged skin ■ with a heating pad

■ on a child under 12 years of age with arthritis like conditions

When using this product

■ avoid contact with eyes or mucous membranes ■ do not bandage tightly

Stop use and ask a doctor if

■ condition worsens, or symptoms persist for more than 7 days ■ symptoms clear up and occur again within a few days

■ excessive skin irritation occurs

Keep out of reach of children

to avoid accidental ingestion. If swallowed, get medical help or contact a Poison Control Center immediately.

Directions

■ use only as directed ■ adults and children 12 years of age and older: apply to affected area not more than 3 to 4 time daily

■ children under 12 years of age: ask a doctor

Other information

■ store between 20 to 25C (68 to 77F) ■ do not use if tube seal under cap is broken, missing or if the tube tip is cut prior to opening

Inactive ingredients

carbomer 940, edetate disodium, glyceryl stearate se, lanolin, polysorbate 80, potassium hydroxide, purified water, stearic acid, trolamine